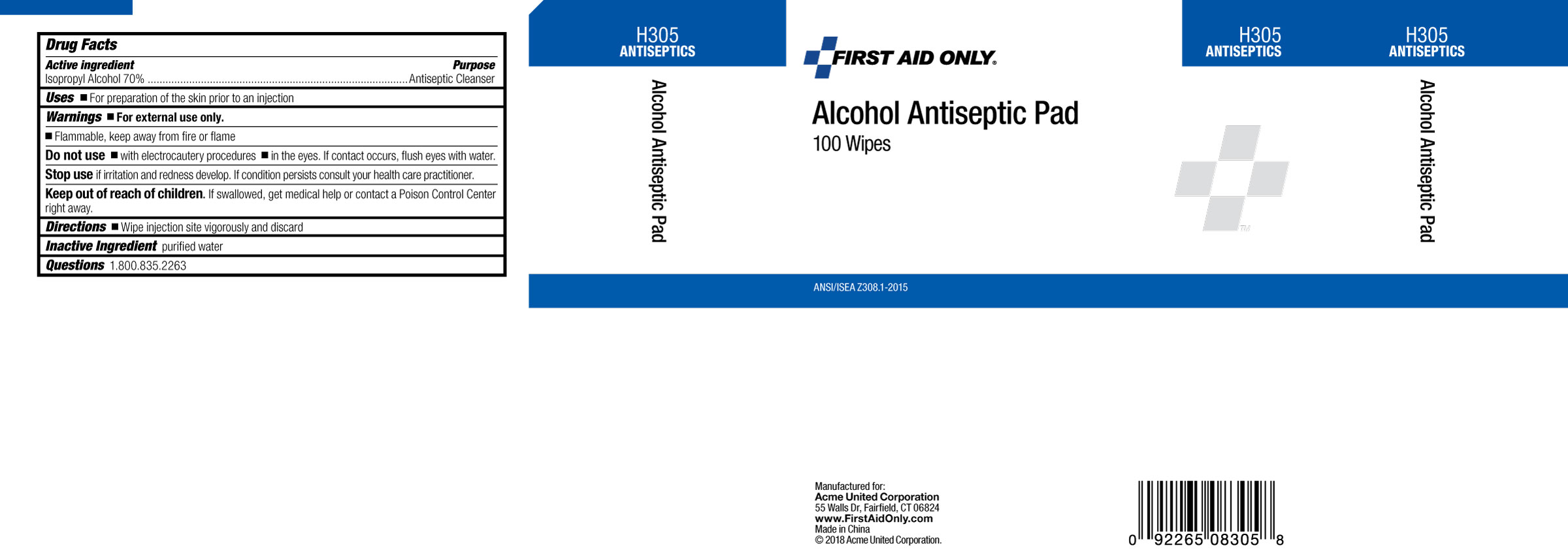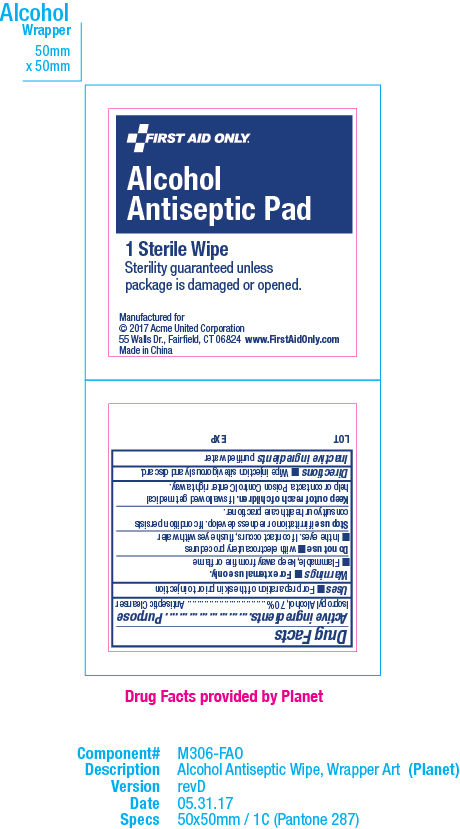 DRUG LABEL: First Aid Only Alcohol Antiseptic Pad
NDC: 0924-0009 | Form: SWAB
Manufacturer: Acme United Corporation
Category: otc | Type: HUMAN OTC DRUG LABEL
Date: 20241126

ACTIVE INGREDIENTS: ISOPROPYL ALCOHOL 70 g/100 g
INACTIVE INGREDIENTS: WATER

First Aid Only Alcohol Antiseptic Pad

Active Ingredients

Active Ingredients Isopropyl Alcohol 70%

Purpose

Antispetic Cleanser

Uses

Uses •For preparation of the skin prior to injection

Warnings

Warnings • For external use only.
•Flammable, keep away from fire or flame

Do not use • with electrocautery procedures

•In the eyes. If contact occurs, flush eyes with water

Stop use

Stop Use if irritation or redness develop.If condition persists consult your health care practicioner.

Keep out of reach of children. If swallowed get medical help or contact a Poison Control Center right away.

Directions

Directions •Wipe Injection site vigorously and discard.

Inactive Ingredients

Inactive Ingredients purified water